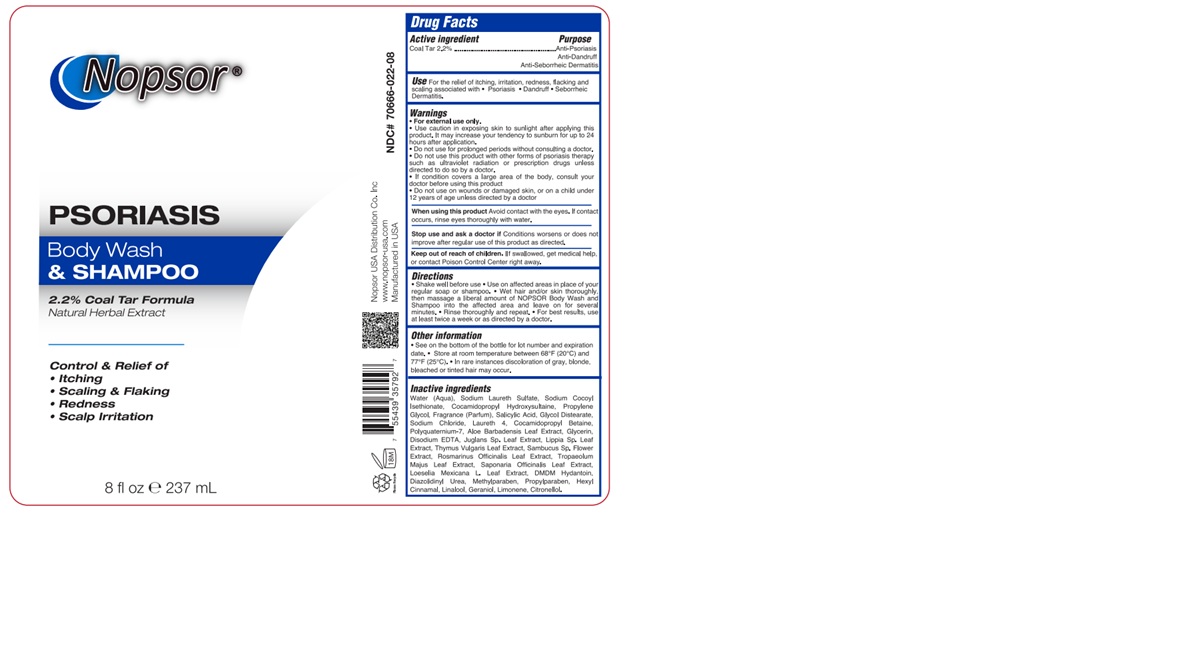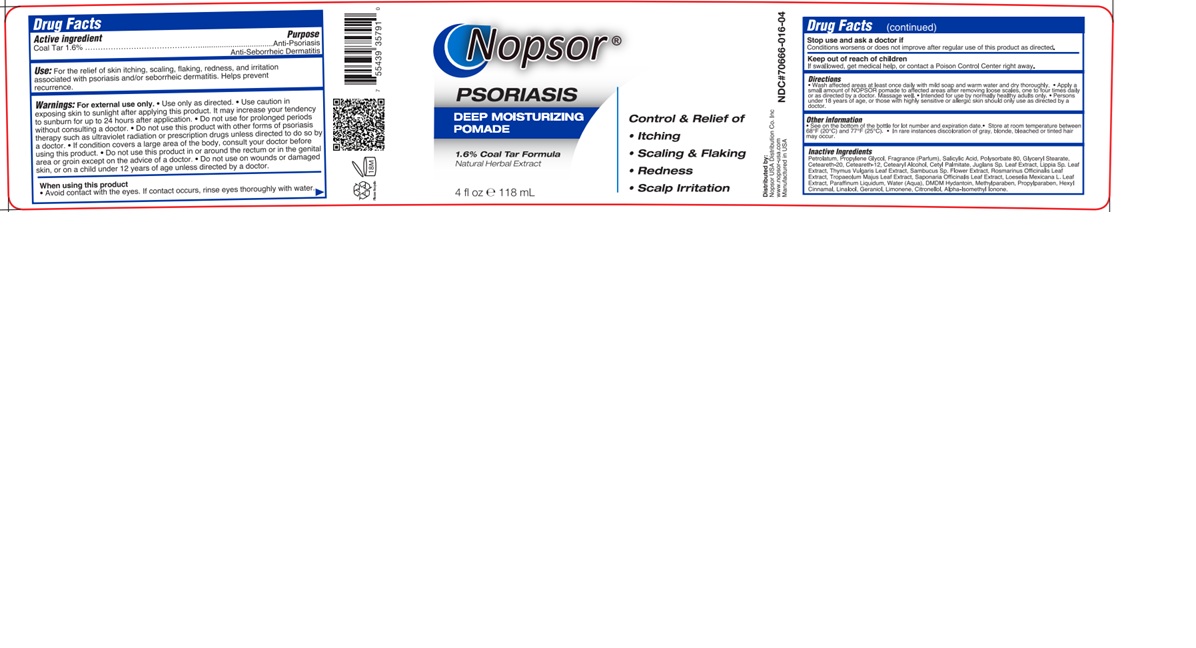 DRUG LABEL: Coal Tar
NDC: 70666-016 | Form: OINTMENT
Manufacturer: Nopsor USA Distribution Co., Inc.
Category: otc | Type: HUMAN OTC DRUG LABEL
Date: 20250505

ACTIVE INGREDIENTS: COAL TAR 1.39 g/100 mL
INACTIVE INGREDIENTS: PARAFFINUM LIQUIDUM; WATER; CETOSTEARYL ALCOHOL; DMDM HYDANTOIN; JUGLANS NIGRA LEAF; LIPPIA GRAVEOLENS LEAF; THYMUS VULGARIS LEAF; SAMBUCUS NIGRA FLOWER; ROSMARINUS OFFICINALIS WHOLE; LOESELIA MEXICANA TOP; .ALPHA.-HEXYLCINNAMALDEHYDE; LINALOOL, (+/-)-; GERANIOL; .BETA.-CITRONELLOL, (R)-; GLYCERYL STEARATE SE; CETYL PALMITATE; METHYLPARABEN; PROPYLPARABEN; POLYSORBATE 80; PROPYLENE GLYCOL; SALICYLIC ACID; LIMONENE, (+)-; POLYOXYL 20 CETOSTEARYL ETHER; CETEARETH-12; TROPAEOLUM MAJUS; SAPONARIA OFFICINALIS LEAF; ALPHA-ISOMETHYL IONONE; PETROLATUM

70666-016-04
70666-022-08

NOPSOR PSORIASIS POMADE

ACTIVE INGREDIENT

Coal Tar 1.6%

PURPOSE

Anti-Psoriasis

Anti-Seborrheic Dermatitis

Use

For the relief of skin itching, scaling, flaking, redness, and irritation associated with psoriasis and/or seborrheic dermatitis. Helps prevent recurrence.

WARNINGS

■ For external use only.

■ Use only as directed.

■ Use caution in exposing skin to sunlight after applying this product. It may increase your tendency to sunburn for up to 24 hours after application.

■ Do not use for prolonged periods without consulting a doctor.

■ Do not use this product with other forms of psoriasis therapy such as ultraviolet radiation or prescription drugs unless directed to do so by a doctor.

■ If condition covers a large area of the body, consult your doctor before using this product.

■ Do not use this product in or around the rectum or in the genital area or groin except on the advice of a doctor.

■ Do not use on wounds or damaged skin, or on a child under 12 years of age unless directed by a doctor.

When using this product

Avoid contact with the eyes. If contact occurs, rinse eyes thoroughly with water

Stop use and ask a doctor if

Conditions worsens or does not improve after regular use of this product as directed

Keep out of reach of children. If swallowed, get medical help or contact a Poison Control Center immediately.

Directions

■ Wash affected areas at least once daily with mild soap and warm water and dry thoroughly.

■ Apply a small amount of NOPSOR pomade to affected areas after removing loose scales, one to four times daily or as directed by a doctor. Massage well.

■ Intended for use by normally healthy adults only.

■ Persons under 18 years of age, or those with highly sensitive or allergic skin should only use as directed by a doctor.

Other information

■ See on the bottom of the bottle for lot number and expiration date.

■ Store at room temperature between 68°F (20°C) and 77°F (25°C).

■ In rare instances discoloration of gray, blonde, bleached or tinted hair may occur.

INACTIVE INGREDIENT

Petrolatum, Propylene Glycol, Fragrance (Parfum), Salicylic Acid, Polysorbate 80, Glyceryl Stearate, Ceteareth-20, Ceteareth-12, Cetearyl Alcohol, Cetyl Palmitate, Juglans Sp. Leaf Extract, Lippia Sp. Leaf Extract, Thymus Vulgaris Leaf Extract, Sambucus Sp. Flower Extract, Rosmarinus Officinalis Leaf Extract, Tropaeolum Majus Leaf Extract, Saponaria Officinalis Leaf Extract, Loeselia Mexicana L. Leaf Extract, Paraffinum Liquidum, Water (Aqua), DMDM Hydantoin, Methylparaben, Propylparaben, Hexyl Cinnamal, Linalool, Geraniol, Limonene, Citronellol, Alpha-Isomethyl Ionone.

NOPSOR PSORIASIS BODY WASH & SHAMPOO

ACTIVE INGREDIENT

Coal Tar 2.2%

PURPOSE

Anti-Psoriasis

Anti-Dandruff

Anti-Seborrheic Dermatitis

Use

For the relief of itching, irritation, redness, flacking and scaling associated with ■ Psoriasis ■ Dandruff ■ Seborrheic Dermatitis.

WARNINGS

■ For external use only.

■ Use caution in exposing skin to sunlight after applying this product. It may increase your tendency to sunburn for up to 24 hours after application.

■ Do not use for prolonged periods without consulting a doctor.

■ Do not use this product with other forms of psoriasis therapy such as ultraviolet radiation or prescription drugs unless directed to do so by a doctor.

■ If condition covers a large area of the body, consult your doctor before using this product

■ Do not use on wounds or damaged skin, or on a child under 12 years of age unless directed by a doctor.

When using this product

Avoid contact with the eyes. If contact occurs, rinse eyes thoroughly with water

Stop use and ask a doctor if

Conditions worsens or does not improve after regular use of this product as directed

Keep out of reach of children. If swallowed, get medical help or contact a Poison Control Center immediately.

Directions

■ Shake well before use

■ Use on affected areas in place of your regular soap or shampoo.

■ Wet hair and/or skin thoroughly, then massage a liberal amount of NOPSOR Body Wash and Shampoo into the affected area and leave on for several minutes.

■ Rinse thoroughly and repeat.

■ For best results, use at least twice a week or as directed by a doctor.

Other information

■ See on the bottom of the bottle for lot number and expiration date.

■ Store at room temperature between 68°F (20°C) and 77°F (25°C).

■ In rare instances discoloration of gray, blonde, bleached or tinted hair may occur.

INACTIVE INGREDIENT

Water (Aqua), Sodium Laureth Sulfate, Sodium Cocoyl Isethionate, Cocamidopropyl Hydroxysultaine, Propylene Glycol, Fragrance (Parfum), Salicylic Acid, Glycol Distearate, Sodium Chloride, Laureth 4, Cocamidopropyl Betaine, Polyquaternium-7, Aloe Barbadensis Leaf Extract, Glycerin, Disodium EDTA, Juglans Sp. Leaf Extract, Lippia Sp. Leaf Extract, Thymus Vulgaris Leaf Extract, Sambucus Sp. Flower Extract, Rosmarinus Officinalis Leaf Extract, Tropaeolum Majus Leaf Extract, Saponaria Officinalis Leaf Extract, Loeselia Mexicana L. Leaf Extract, DMDM Hydantoin, Diazolidinyl Urea, Methylparaben, Propylparaben, Hexyl Cinnamal, Linalool, Geraniol, Limonene, Citronellol.